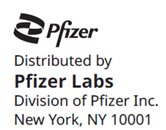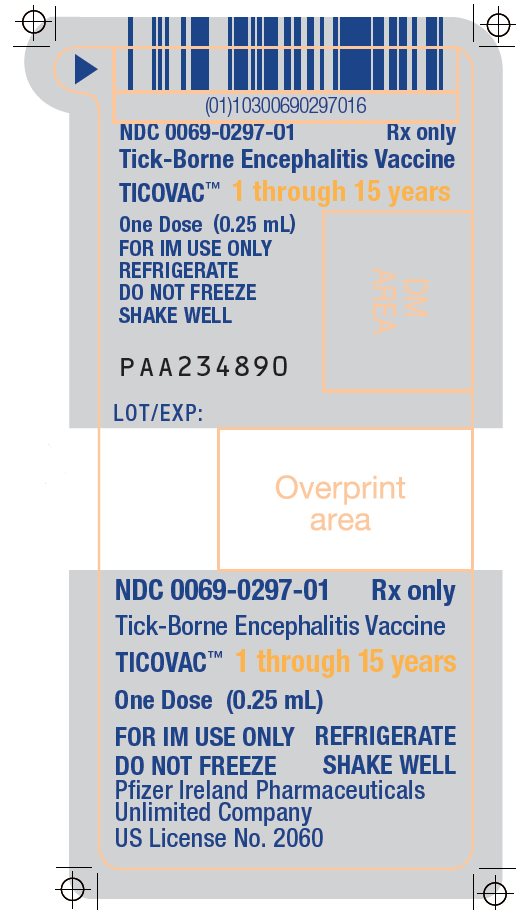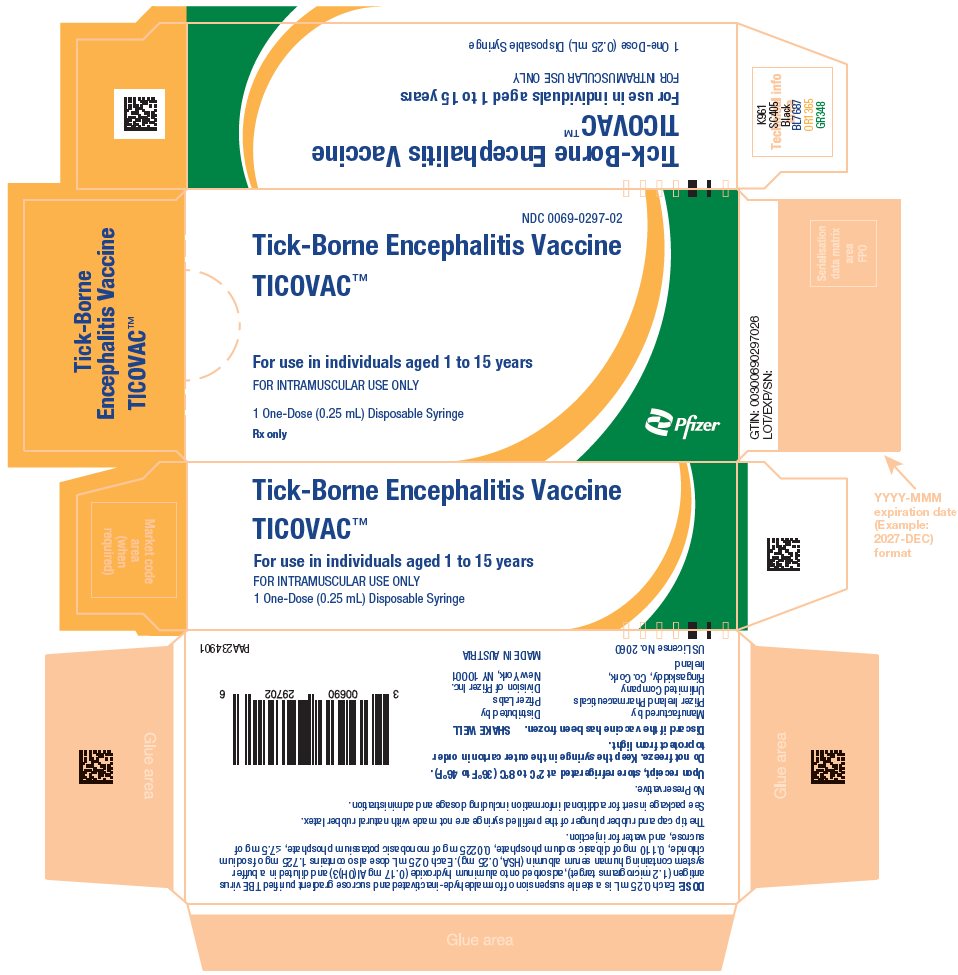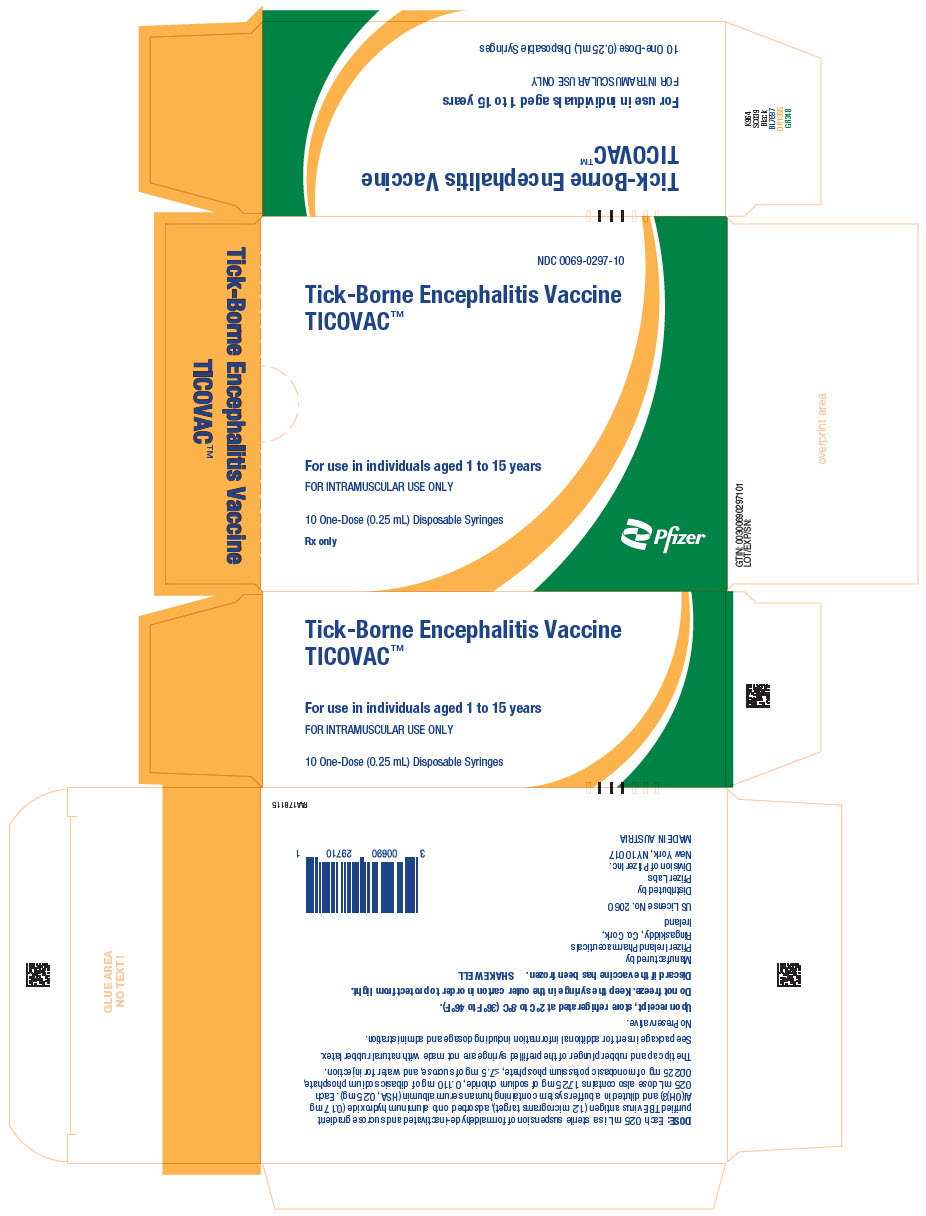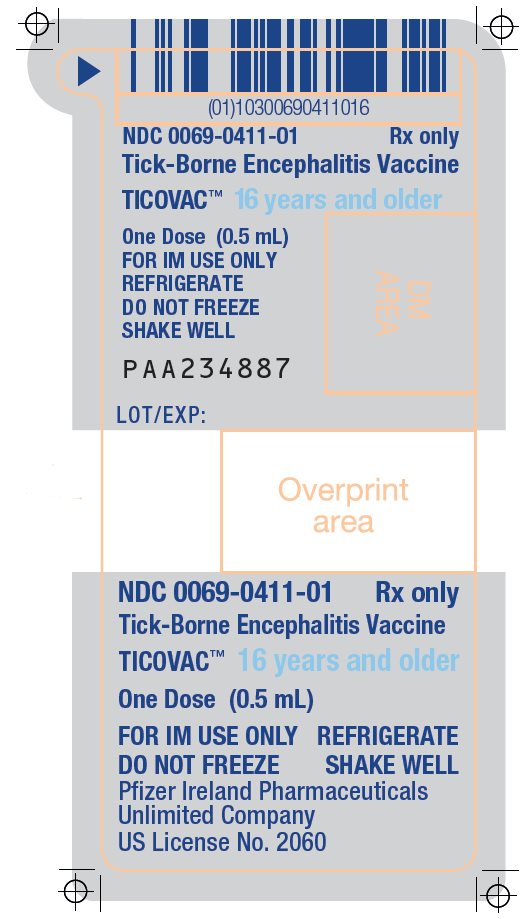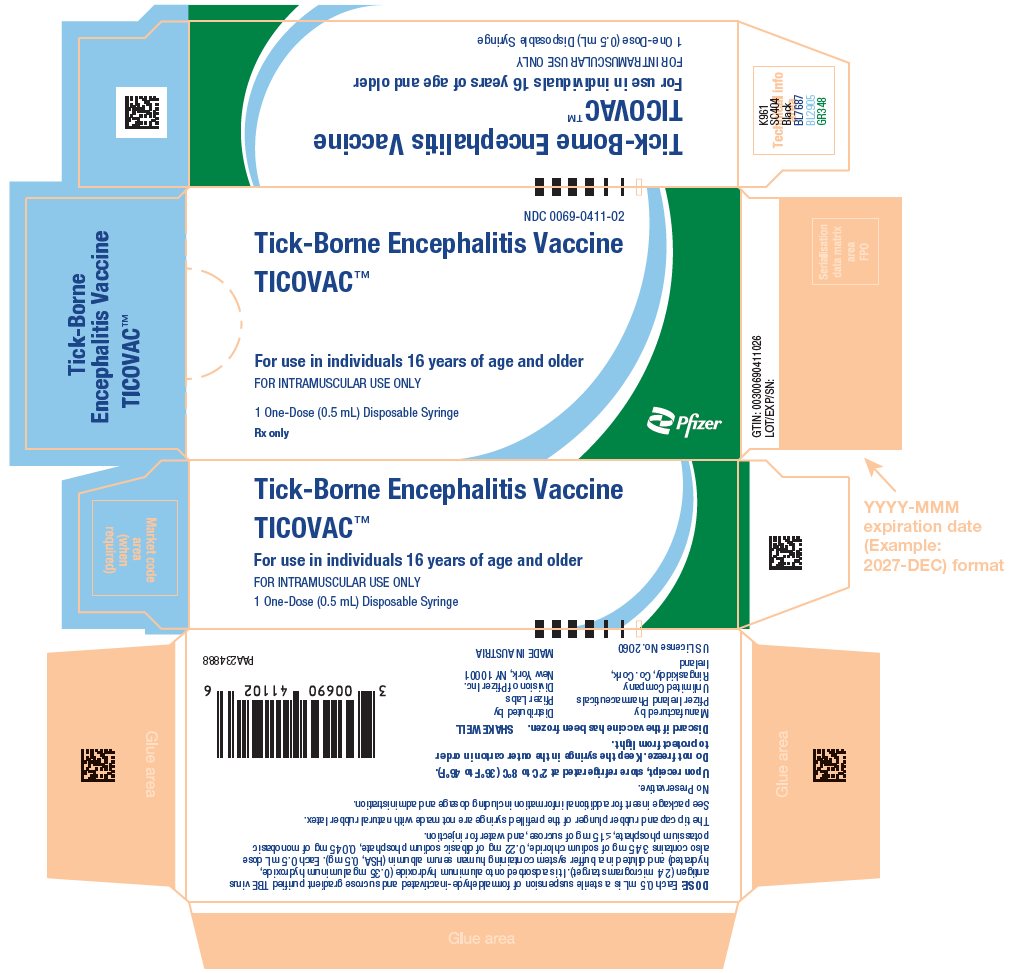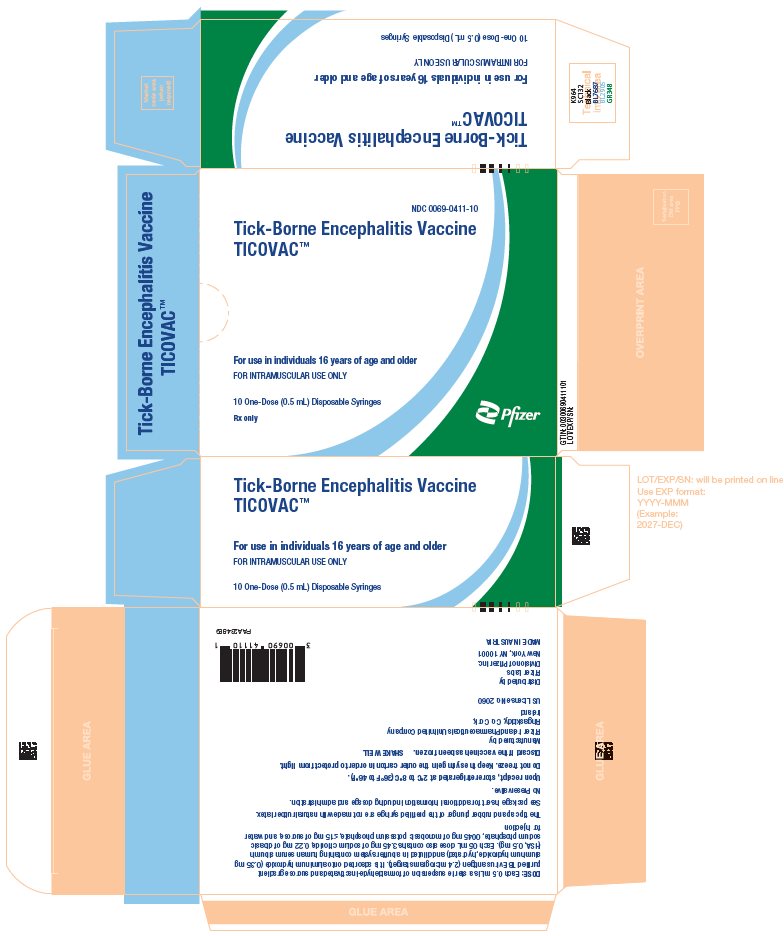 DRUG LABEL: TicoVac
NDC: 0069-0297 | Form: INJECTION
Manufacturer: Pfizer Laboratories Div Pfizer Inc
Category: other | Type: VACCINE LABEL
Date: 20250912

ACTIVE INGREDIENTS: TICK-BORNE ENCEPHALITIS PURIFIED ANTIGEN (FORMALDEHYDE INACTIVATED) 1.2 ug/0.25 mL
INACTIVE INGREDIENTS: SODIUM CHLORIDE 1.725 mg/0.25 mL; SODIUM PHOSPHATE, DIBASIC, DIHYDRATE 0.11 mg/0.25 mL; MONOBASIC POTASSIUM PHOSPHATE 0.0225 mg/0.25 mL; WATER; ALGELDRATE 0.175 mg/0.25 mL; ALBUMIN HUMAN 0.25 mg/0.25 mL

HIGHLIGHTS OF PRESCRIBING INFORMATION

These highlights do not include all the information needed to use TICOVAC safely and effectively. See full prescribing information for TICOVAC.
TICOVAC (Tick-Borne Encephalitis Vaccine), Suspension for intramuscular injection
Initial U.S. Approval: 2021

1 INDICATIONS AND USAGE

TICOVAC is a vaccine indicated for active immunization to prevent tick-borne encephalitis (TBE). TICOVAC is approved for use in individuals 1 year of age and older. (1)

2 DOSAGE AND ADMINISTRATION

For intramuscular use only.

- 1 through 15 years of age: each dose 0.25 mL
- 16 years of age and older: each dose 0.5 mL

Primary Vaccination: Three doses (2.1)

Primary Vaccination Schedule
 | 1 through 15 years of age | 16 years of age and older
First dose | Day 0 | Day 0
Second dose | 1 to 3 months after the first vaccination | 14 days to 3 months after the first vaccination
Third dose | 5 to 12 months after the second vaccination | 5 to 12 months after the second vaccination

A booster dose (fourth dose) may be given at least 3 years after completion of the primary immunization series if ongoing exposure or re-exposure to tick-borne encephalitis virus (TBEV) is expected.

3 DOSAGE FORMS AND STRENGTHS

Suspension for injection supplied as a 0.25 mL or 0.5 mL single-dose in pre-filled syringes. (3)

4 CONTRAINDICATIONS

- Severe allergic reaction (e.g. anaphylaxis) to any component of TICOVAC. (4)

6 ADVERSE REACTIONS

The most common adverse reactions are as follows:

- 1 through 15 years of age: Local tenderness (18.1%), local pain (11.2%), headache (11.1%), fever (9.6%), and restlessness (9.1%). (6.1)
- 16 through 65 years of age: Local tenderness (29.9%), local pain (13.2%), fatigue (6.6%), headache (6.3%), and muscle pain (5.1%). (6.1)

To report SUSPECTED ADVERSE REACTIONS, contact Pfizer Inc. at 1-800-438-1985 or VAERS at 1-800-822-7967 or http://vaers.hhs.gov.

FULL PRESCRIBING INFORMATION

1 INDICATIONS AND USAGE

TICOVAC™ is indicated for active immunization to prevent tick-borne encephalitis (TBE). TICOVAC is approved for use in individuals 1 year of age and older.

2 DOSAGE AND ADMINISTRATION

For intramuscular use only.

2.1 Dosage and Vaccination Schedule

- 1 through 15 years of age: each dose 0.25 mL
- 16 years of age and older: each dose 0.5 mL

Primary Vaccination: Three doses

Table 1: Primary Vaccination Schedule - TICOVAC
 | 1 through 15 years of age | 16 years of age and older
First dose | Day 0 | Day 0
Second dose | 1 to 3 months after the first vaccination | 14 days to 3 months after the first vaccination
Third dose | 5 to 12 months after the second vaccination | 5 to 12 months after the second vaccination

Complete the primary immunization series at least 1 week prior to potential exposure to TBEV (tick-borne encephalitis virus) [see Clinical Studies (14.1)].

A booster dose (fourth dose) may be given at least 3 years after completion of the primary immunization series if ongoing exposure or re-exposure to TBEV is expected.

2.2 Administration

Bring the vaccine to room temperature before administration. Shake well prior to administration to thoroughly mix the vaccine suspension. After shaking, the vaccine should be a homogenous off-white, opalescent suspension. Parenteral drug products should be inspected visually for particulate matter and discoloration prior to administration, whenever solution and container permit. Do not administer if particulate matter or discoloration remains after shaking. Administer vaccine by intramuscular injection.

3 DOSAGE FORMS AND STRENGTHS

TICOVAC is a suspension for injection supplied as a 0.25 mL or 0.5 mL single-dose in pre-filled syringes.

4 CONTRAINDICATIONS

Severe allergic reaction (e.g. anaphylaxis) to any component of TICOVAC [see Description (11)].

5 WARNINGS AND PRECAUTIONS

5.1 Management of Acute Allergic Reactions

Appropriate medical treatment and supervision must be available to manage possible anaphylactic reactions following administration of TICOVAC.

5.2 Altered Immunocompetence

Some individuals with altered immunocompetence may have reduced immune responses to TICOVAC.

5.3 Human Albumin

TICOVAC contains albumin, a derivative of human blood. Based on effective donor screening and product manufacturing processes, it carries an extremely remote risk for transmission of viral diseases and variant Creutzfeldt-Jakob disease (vCJD). There is a theoretical risk for transmission of Creutzfeldt-Jakob disease (CJD), but if that risk actually exists, the risk of transmission would also be considered extremely remote. No cases of transmission of viral diseases, CJD or vCJD have ever been identified for licensed albumin or albumin contained in other licensed products.

5.4 Limitation of Vaccine Effectiveness

Vaccination with TICOVAC may not protect all individuals.

6 ADVERSE REACTIONS

In clinical studies, the most common adverse reactions in subjects 1 through 15 years of age who received TICOVAC were local tenderness (18.1%), local pain (11.2%), headache (11.1%), fever (9.6%), and restlessness (9.1%).

The most common adverse reactions in subjects 16 through 65 years of age who received TICOVAC were local tenderness (29.9%), local pain (13.2%), fatigue (6.6%), headache (6.3%), and muscle pain (5.1%).

6.1 Clinical Trials Experience

Because clinical trials are conducted under widely varying conditions, adverse reaction rates observed in the clinical trials of a vaccine cannot be directly compared to rates in the clinical trials of another vaccine and may not reflect the rates observed in practice.

Among a total of 10 clinical trials, 3240 healthy children 1 through 15 years of age received at least one dose of TICOVAC. A total of 4427 healthy adults 16 years of age and older received at least one dose of TICOVAC in 10 clinical trials.

Study 209 was a multicenter, open-label study to investigate the safety of TICOVAC in 2,417 healthy children 1 through 15 years of age who received three vaccinations (Day 0, 1 and 6 months after the first vaccination). The incidence rates for local and systemic solicited adverse reactions within 4 days after each dose are presented in Table 2.

Table 2: Incidence Rates of Solicited Local and Systemic Adverse Reactions Within 4 Days After Each Dose of TICOVAC, Children 1 through 15 Years of Age (Study 209)
 |  | Percentage (%) of Subjects
Age Group [Some symptoms were solicited using different terms in younger and older children, to be age appropriate.] | Adverse Reaction | Dose 1 N=2417 | Dose 2 N=2410 | Dose 3 N=2390
Local Reaction
1–15 Years | Tenderness | 18.1 | 12.9 | 13.3
1–15 Years | Local pain | 11.2 | 7.9 | 9.7
1–15 Years | Erythema | 3.0 | 1.5 | 2.8
1–15 Years | Induration | 2.2 | 1.3 | 2.1
1–15 Years | Swelling | 1.9 | 1.1 | 2.5
1–15 Years | Itching | <0.1 | <0.1 | 0
1–15 Years | Ecchymosis | 0 | 0 | <0.1
1–15 Years | Hematoma | <0.1 | 0 | 0
Systemic Reaction
1–15 Years | Fever | 9.6 | 2.3 | 2.4
1–15 Years | Headache | 11.1 | 3.9 | 3.4
1–15 Years | Muscle pain | 3.6 | 2.0 | 1.8
1–15 Years | Loss of appetite | 3.1 | 1.5 | 1.2
1–15 Years | Nausea | 3.3 | 1.0 | 0.8
1–15 Years | Changes in sleeping behavior | 2.8 | 1.0 | 0.8
1–15 Years | Vomiting | 1.7 | 0.7 | 0.3
1–15 Years | Joint pain | 1.2 | 0.6 | 0.5
1–15 Years | Swelling of the axillary /inguinal lymph nodes | 0.2 | 0.3 | 0.2
 |  | N=584 | N=581 | N=576
1–5 Years | Restlessness | 9.1 | 3.6 | 3.5
 |  | N=1833 | N=1829 | N=1814
6–15 Years | Fatigue | 6.3 | 2.4 | 2.5
 | Malaise | 4.8 | 1.6 | 1.8
Abbreviation: N=total number of subjects who received TICOVAC at each dose for each age group.
Clinical trial identifier: NCT 00161863.

Incidence rates of fever reported within 4 days after each dose of TICOVAC, by age group, in Study 209 are presented in Table 3.

Table 3: Fever Rates Within 4 Days After Each Dose of TICOVAC by Age Group (Study 209)
Dose Age Group | Percentage (%) of Subjects
Dose Age Group | 38.0–38.4°C (100.4–101.1°F) | 38.5–38.9°C (101.2–102.0°F) | 39.0–40.0°C (102.1–104°F) | >40°C (>104°F)
Dose 1
1–2 Years of Age (N=186) | 23.7 | 5.9 | 5.9 | 0
3–6 Years of Age (N=563) | 4.6 | 5.0 | 3.0 | 0
7–15 Years of Age (N=1668) | 3.4 | 2.0 | 0.3 | 0
Total (N=2417) | 5.2 | 3.0 | 1.4 | 0
Dose 2
1–2 Years of Age (N=185) | 9.2 | 2.2 | 0.5 | 0.5
3–6 Years of Age (N=561) | 1.2 | 0.4 | 0.5 | 0
7–15 Years of Age (N=1664) | 0.8 | 0.4 | <0.1 | 0
Total (N=2410) | 1.6 | 0.5 | 0.2 | <0.1
Dose 3
1–2 Years of Age (N=184) | 7.1 | 3.8 | 1.6 | 0
3–6 Years of Age (N=557) | 1.4 | 0.4 | 0.7 | 0.2
7–15 Years of Age (N=1649) | 0.6 | 0.3 | 0.2 | 0
Total (N=2390) | 1.3 | 0.6 | 0.5 | <0.1
Abbreviation: N=total number of subjects who received TICOVAC at each dose for each age group.
Clinical trial identifier: NCT 00161863.

The following additional adverse reactions to the vaccine have been reported in <1% of subjects 1 through 15 years of age who received TICOVAC in clinical trials (N=3240): vertigo, dizziness, sensory abnormalities, abdominal pain, diarrhea, dyspepsia, injection site pruritus, and urticaria.

Study 208 was a randomized, comparative, single-blind study that assessed the safety of TICOVAC. Healthy subjects 16 through <65 years of age (N=3966) were randomized 3:1 to receive two vaccinations with either TICOVAC or a non-US licensed TBE vaccine comparator administered 21 to 35 days apart. Study 213 was an open-label follow-up study to Study 208; all subjects who had received two vaccinations in Study 208 (regardless of which vaccine they had received) were eligible and received a third vaccination with TICOVAC 6 months after the first vaccination in Study 208 (N=3705).

Incidence rates of solicited local and systemic adverse reactions reported in Study 208 (Doses 1 and 2) and Study 213 (Dose 3) are presented in Table 4.

Table 4: Incidence Rates of Specifically Solicited Local and Systemic Adverse Reactions Within 4 Days After Each Dose of TICOVAC, Subjects 16 through <65 Years of Age (Study 208/213)
 | Percentage (%) of Subjects
Adverse Reaction | Dose 1 N=2977 [N=total number of subjects who received 1 dose of TICOVAC in Study 208.] | Dose 2 N=2950 [N=total number of subjects who received 2 doses of TICOVAC in Study 208.] | Dose 3 [N=total number of subjects who received 2 doses of TICOVAC in Study 208 and received TICOVAC in Study 213.] N=2790
Local Reaction
Tenderness | 29.9 | 27.4 | 25.7
Local pain | 13.2 | 13.5 | 12.0
Erythema | 3.6 | 2.3 | 3.4
Induration | 2.0 | 1.5 | 2.6
Swelling | 1.6 | 1.4 | 2.0
Hematoma | <0.1 | <0.1 | 0.1
Ecchymosis | <0.1 | 0 | <0.1
Systemic Reaction
Fever | 0.8 | 0.5 | 0.5
Fatigue | 6.6 | 4.1 | 5.3
Headache | 6.3 | 4.4 | 4.9
Muscle pain | 5.1 | 3.7 | 3.8
Malaise | 4.9 | 3.3 | 3.7
Joint pain | 1.4 | 1.1 | 1.4
Nausea | 2.1 | 0.9 | 1.0
Swelling of the lymph nodes | 0.6 | 0.3 | 0.7
Vomiting | 0.2 | 0.1 | <0.1
Clinical trial identifiers: NCT00161824 and NCT00161876.

The following additional adverse reactions have been reported in <1% of subjects 16 through <65 years of age who received TICOVAC in clinical trials (N=4427): hypersensitivity, somnolence, vertigo, diarrhea, abdominal pain, injection site pruritus, and injection site warmth.

Subjects who were seropositive either by ELISA or NT 1 month after the third dose in Studies 209 and 208/213, were invited to participate in follow-up Studies 700401 and 223 (studies assessing antibody persistence and response to a booster dose at 3 years), respectively. A total of 156 subjects received a fourth dose of TICOVAC (0.25 mL), and 240 subjects received a fourth dose of TICOVAC (0.5 mL) in these clinical trials.

Incidence rates of solicited local and systemic adverse reactions reported in Study 223 and 70401 after the booster are presented in Table 5.

Table 5: Incidence Rates of Specifically Solicited Symptoms of Local and Systemic Adverse Reactions Within 4 Days After 4th Dose of TICOVAC
 |  | Percentage (%) of Subjects
 |  | Study 223 (N [N=total number of subjects who received 4 doses of TICOVAC (0.5 mL) in Studies 208/213 and 223.] =240) TICOVAC (0.5 mL) | Study 700401 (N [N=total number of subjects who received 4 doses of TICOVAC (0.25 mL) in Studies 209 and 700401.] =156) TICOVAC (0.25 mL)
Local Reaction | Tenderness | 4.6 | 10.3
 | Injection Site Pain | 3.8 | 14.7
 | Erythema | 0.4 | 1.3
 | Induration | 0.4 | 3.2
 | Swelling | 0.8 | 3.2
 | Hematoma | 0 | 0
 | Ecchymosis | 0 | 0
Systemic Reaction | Fever | 0 | 0
 | Fatigue | 0 | 0.6
 | Headache | 0.4 | 3.2
 | Muscle Pain | 0.4 | 3.2
 | Malaise | 0.4 | 1.3
 | Joint Pain | 0 | 1.3
 | Nausea | 0 | 0.6
 | Swelling of the Lymphnodes | 0 | 0
 | Vomiting | 0 | 0
 | Loss of Appetite | NA | 1.9
 | Changes in sleeping behavior | NA | 0
Abbreviation: NA=not applicable.
Note: Solicited symptoms with onset date between Day 0 (vacciantion day) and Day 4 were included in the analysis.

Among 3240 subjects who received TICOVAC (0.25 mL) in clinical trials, serious adverse events (SAEs) and death were reported in 62 subjects and 1 subject, respectively. Among 4427 subjects who received TICOVAC (0.5 mL) in clinical trials, SAEs and deaths were reported in 54 subjects and 2 subjects, respectively. None of these events was considered related to the vaccine. Only one SAE in TICOVAC (0.25 mL) was considered possibly related to vaccine (febrile convulsion reported in a 12-month old male two days after vaccination in Study 197, a postmarketing safety surveillance study).

6.2 Postmarketing Experience

The following adverse reactions have been reported spontaneously (postmarketing) with the use of TICOVAC in the European Union (EU). Because these reactions are reported voluntarily from a population of uncertain size, it is not always possible to reliably estimate their frequency or establish a causal relationship to vaccine exposure.

- Infections and infestations: herpes zoster (triggered in pre-exposed individuals)
- Immune system disorders: anaphylactic reaction, hypersensitivity, precipitation or aggravation of autoimmune disorders (e.g., multiple sclerosis)
- Nervous system disorders: convulsion, convulsion (including febrile), demyelinating disorders (acute disseminated encephalomyelitis, Guillain-Barré syndrome, myelitis, transverse myelitis), encephalitis, sensory abnormalities and motor dysfunction (hemiparesis, hemiplegia, VIIth nerve paralysis/facial paresis, paralysis, paresis, neuritis, neuralgia, optic neuritis), polyneuropathy, meningism, dizziness, aseptic meningitis
- Eye disorders: visual impairment, photophobia, eye pain
- Ear and labyrinth disorders: tinnitus
- Cardiac disorders: tachycardia
- Respiratory, thoracic and mediastinal disorders: dyspnea
- Skin and subcutaneous tissue disorders: urticaria, rash (erythematous, maculo-papular, vesicular), pruritus, dermatitis, erythema, hyperhidrosis
- Musculoskeletal and connective tissue disorders: back pain, joint swelling, neck pain, musculoskeletal stiffness (including neck stiffness), pain in extremity
- General disorders and administration site conditions: injection site joint movement impairment, injection site joint pain, injection site nodule, injection site inflammation, influenza-like illness, chills, gait disturbance, asthenia, edema

8 USE IN SPECIFIC POPULATIONS

8.1 Pregnancy

Risk Summary

All pregnancies have a risk of birth defect, loss, or other adverse outcomes. In the US general population, the estimated background risk of major birth defects and miscarriage in clinically recognized pregnancies is 2% to 4% and 15% to 20%, respectively. There are no adequate and well-controlled studies of TICOVAC in pregnant women. Available human data are insufficient to establish the presence or absence of vaccine-associated risk during pregnancy.

Developmental and reproductive toxicity studies in animals have not been conducted with TICOVAC.

8.2 Lactation

Risk Summary

Human data are not available to assess the impact of TICOVAC on milk production, its presence in breast milk, or its effects on the breastfed. The developmental and health benefits of breastfeeding should be considered along with the mother's clinical need for TICOVAC and any potential adverse effects on the breastfed child from TICOVAC or from the underlying maternal condition. For preventive vaccines, the underlying maternal condition is susceptibility to disease prevented by the vaccine.

8.4 Pediatric Use

Safety and effectiveness of TICOVAC have not been established in infants below 1 year of age.

8.5 Geriatric Use

Clinical studies of TICOVAC did not include sufficient numbers of subjects aged 65 and over to determine whether they respond differently from younger subjects. A clinical study (Study 690601, NCT00460486) of TICOVAC enrolled 73 subjects 60 years of age and older, including 31 subjects 65 years of age and older.

11 DESCRIPTION

TICOVAC (tick-borne encephalitis vaccine) is a sterile, off-white, homogenous, opalescent suspension for intramuscular injection. TICOVAC is prepared from tick-borne encephalitis (TBE) virus propagated in chick embryo fibroblast (CEF) cells. The harvested virus suspension is inactivated by treatment with formaldehyde, purified by sucrose gradient centrifugation and adsorbed onto aluminum hydroxide. TICOVAC is available in a 0.5 mL adult presentation and a 0.25 mL pediatric presentation.

Each 0.5 mL dose is formulated to contain 2.4 microgram (µg) TBE inactivated virus, 0.5 mg human serum albumin, 0.35 mg aluminum hydroxide, 3.45 mg sodium chloride, 0.22 mg dibasic sodium phosphate, and 0.045 mg of monobasic potassium phosphate. From the manufacturing process, each 0.5 mL may also contain formaldehyde (≤5 µg), sucrose (≤15 mg), protamine sulfate (≤0.5 µg), and trace amounts of chick protein and DNA from CEF cells, neomycin and gentamicin. The 0.25 mL dose of TICOVAC contains the same components as the 0.5 mL dose in half of the quantities.

TICOVAC is formulated without preservatives.

12 CLINICAL PHARMACOLOGY

12.1 Mechanism of Action

Following administration, TICOVAC induces TBEV-neutralizing antibodies, which are believed to confer protection. However, a protective antibody level has not been defined.

13 NONCLINICAL TOXICOLOGY

13.1 Carcinogenesis, Mutagenesis, Impairment of Fertility

TICOVAC has not been evaluated for the potential to cause carcinogenicity, genotoxicity or impairment of fertility.

14 CLINICAL STUDIES

14.1 Immunogenicity

Primary Immunization Course

The immunogenicity of TICOVAC described in this section is based on results from the following studies:

- Study 209: Healthy subjects 1 through 15 years of age TBE seronegative at baseline received three vaccinations with TICOVAC. The first two vaccinations were given 1 month apart followed by the third vaccination 6 months after the first vaccination.
- Study 213: Healthy subjects 16 to 64 years of age TBE seronegative at baseline who had received two vaccinations in Study 208 given one month apart, received a third vaccination with TICOVAC 6 months after the first vaccination in Study 208.
- Study 690601: Healthy subjects 16 years of age and older TBE seronegative at baseline received three vaccinations with TICOVAC. The first two vaccinations were given 14 days apart followed by the third vaccination 6 months after the first vaccination.

Table 6 shows neutralization test (NT) seropositivity rates 21 days after the third vaccination in subjects 1 through 15 years of age vaccinated with TICOVAC in Study 209.

Table 6: Seropositivity Rates (NT) [Seropositivity was defined as NT ≥1:10 (Neudoerfl TBE strain).] by Age Group; Post Dose 3 [Evaluated 21 days after Dose 3.] (Study 209)
Age Group | % (n/N) | (95% CI) [Exact 2-sided CI calculated using the Clopper and Pearson method.]
1–5 Years | 99.2% (125/126) | (95.7%, 100.0%)
6–15 Years | 99.6% (240/241) | (97.7%, 100.0%)
Total | 99.5% (365/367) | (98.0%, 99.9%)
Abbreviations: CI=confidence interval; NT=neutralization test.
Clinical trial identifier: NCT00161863.

Table 7 shows NT seropositivity rates 21 days after the third vaccination in subjects 16 years of age and older vaccinated with TICOVAC in Study 690601 and Study 213.

Table 7: Seropositivity Rates (NT) [Seropositivity was defined as NT ≥1:10 (Neudoerfl TBE strain).] by Age Group; Post Dose 3 [Evaluated 21 days after Dose 3.] TICOVAC (Studies 213 and 690601)
Age Group (Study Number) | % (n/N) | (95% CI) [Exact 2-sided CI calculated using the Clopper and Pearson method.]
16–64 Years (Study 213) | 98.8% (411/416) | (97.2%, 99.6%)
16–49 Years (Study 690601) | 100.0% (144/144) | (97.5%, 100.0%)
≥50 Years (Study 690601) | 98.7% (151/153) | (95.4%, 99.8%)
Abbreviations: CI=confidence interval; NT=neutralization test.
Clinical trial identifiers: NCT00161876 and NCT00460486.

Seven days after the third vaccination, 90.6% of the subjects 16 years of age and older were seropositive (Study 690601).

Seropersistence and Booster Vaccination

Two open-label, multi-center, follow-up studies which enrolled subjects who were seropositive 1 month after the third vaccination from Studies 213 (N=252, ages 16 through 65 at the time of first TICOVAC dose) and 209 (N=358, ages 1 through 15 at the time of first TICOVAC dose) were conducted to assess the seropersistence of TBE antibodies after completion of the primary vaccination series and the antibody response to a booster administration. Three years after the primary series of TICOVAC, NT seropositivity in follow-up studies 223 and 700401 ranged from 82.9% to 100% depending on age. Following a booster dose the NT seropositivity rates were 100%.

14.2 Field Vaccine Effectiveness

In Austria, field effectiveness of TBE vaccines was assessed retrospectively for the period from 2000 to 2011. During this period, two TBE vaccines were available in Austria. The market coverage in Austria for TICOVAC was 95%, 90%, and 80%, in 2000, 2006, and 2011, respectively.^1 The calculation of TBE vaccine effectiveness overall is based on (1) the annual numbers of serologically confirmed cases of TBE virus infections with neurological symptoms causing hospitalization (2) their vaccination history, and (3) the proportion of vaccinated and unvaccinated in the Austrian population. During the study period, the recommended vaccination schedule in Austria consisted of 2 vaccinations approximately 4 weeks apart followed by a third vaccination 5–12 months after the second dose, and a booster vaccination ≥3 years after the third dose. The TBE cases were categorized based on their vaccination status. Among the 883 TBE cases in Austria between 2000 and 2011, 45 patients did not have an accurate vaccination history. The best-case and worst-case estimates of vaccine effectiveness were calculated. For the best-case estimate, the 45 patients without an accurate vaccination history were excluded from the calculation. For the worst-case estimate, these 45 patients were assumed to have been vaccinated according to the recommended schedule. The proportions of vaccinated and unvaccinated individuals in the general population were estimated using annual postal surveys sent to 4,000 households (8,500–10,000 household members). Overall, worst-case and best-case TBE vaccine effectiveness for preventing hospitalized TBE was estimated to be 96.3% (95% CI: 95.5, 97.0) and 98.7% (95% CI: 98.2, 99.0), respectively, following at least 3 doses of TBE vaccine administered according to the recommended schedule in Austria.^2

15 REFERENCES

1. Heinz FX, Holzmann H, Essl A, et al. Field effectiveness of vaccination against tick-borne encephalitis. Vaccine 2007;25(43):7559–67.
2. Heinz FX, Stiasny K, Holzmann H, et al. Vaccination and tick-borne encephalitis, central Europe. Emerg Infect Dis 2013;19(1):69–76.

16 HOW SUPPLIED/STORAGE AND HANDLING

16.1 How Supplied

TICOVAC is supplied in the following strengths and package configurations:

Presentation | Carton NDC | Components
One dose (10 per package) | NDC 0069-0411-10 | 0.5 mL pre-filled syringe
One dose (1 per package) | NDC 0069-0411-02 | 0.5 mL pre-filled syringe
One dose (10 per package) | NDC 0069-0297-10 | 0.25 mL pre-filled syringe
One dose (1 per package) | NDC 0069-0297-02 | 0.25 mL pre-filled syringe

The tip cap and rubber plunger of the pre-filled syringe are not made with natural rubber latex.

16.2 Storage and Handling

Upon receipt, store refrigerated at 2ºC to 8ºC (36ºF to 46ºF).

Keep the syringe in the outer carton in order to protect from light. Do not freeze. Discard if the vaccine has been frozen.

17 PATIENT COUNSELING INFORMATION

Prior to administration of this vaccine, inform the individual, parent, guardian, or other responsible adult of the following:

- The potential benefits and risks of immunization with TICOVAC [see Warnings and Precautions (5), Adverse Reactions (6) and Clinical Studies (14)].
- The importance of completing the approved three dose primary immunization series before potential exposure to TBEV [see Dosage and Administration (2.1)].
- Report any suspected adverse reactions to a healthcare professional.

This product's labeling may have been updated. For the most recent prescribing information, please visit www.pfizer.com.

Manufactured by: Pfizer Ireland Pharmaceuticals
Ringaskiddy,
Co. Cork,
Ireland
US License No. 2060

LAB-1467-2.0

PRINCIPAL DISPLAY PANEL - 0.25 mL Syringe Label

(01)10300690297016

NDC 0069-0297-01
Rx only

Tick-Borne Encephalitis Vaccine

TICOVAC™ 1 through 15 years

One Dose (0.25 mL)

FOR IM USE ONLY
REFRIGERATE
DO NOT FREEZE
SHAKE WELL

Pfizer Ireland Pharmaceuticals
Unlimited Company
US License No. 2060

PAA234890

LOT/EXP:

PRINCIPAL DISPLAY PANEL - 0.25 mL Syringe Carton - 0069-0297-02

NDC 0069-0297-02

Tick-Borne Encephalitis Vaccine

TICOVAC™

For use in individuals aged 1 to 15 years
FOR INTRAMUSCULAR USE ONLY

1 One-Dose (0.25 mL) Disposable Syringe

Rx only

Pfizer

PRINCIPAL DISPLAY PANEL - 0.25 mL Syringe Carton - 0069-0297-10

NDC 0069-0297-10

Tick-Borne Encephalitis Vaccine

TICOVAC™

For use in individuals aged 1 to 15 years
FOR INTRAMUSCULAR USE ONLY

10 One-Dose (0.25 mL) Disposable Syringes

Rx only

Pfizer

PRINCIPAL DISPLAY PANEL - 0.5 mL Syringe Label

(01)10300690411016

NDC 0069-0411-01
Rx only

Tick-Borne Encephalitis Vaccine

TICOVAC™
16 years and older

One Dose (0.5 mL)
FOR IM USE ONLY
REFRIGERATE
DO NOT FREEZE
SHAKE WELL

Pfizer Ireland Pharmaceuticals
Unlimited Company
US License No. 2060

PAA234887

LOT/EXP:

PRINCIPAL DISPLAY PANEL - 0.5 mL Syringe Carton - 0069-0411-02

NDC 0069-0411-02

Tick-Borne Encephalitis Vaccine

TICOVAC™

For use in individuals 16 years of age and older
FOR INTRAMUSCULAR USE ONLY

1 One-Dose (0.5 mL) Disposable Syringe

Rx only

Pfizer

PRINCIPAL DISPLAY PANEL - 0.5 mL Syringe Carton - 0069-0411-10

NDC 0069-0411-10

Tick-Borne Encephalitis Vaccine
TICOVAC™

For use in individuals 16 years of age and older
FOR INTRAMUSCULAR USE ONLY

10 One-Dose (0.5 mL) Disposable Syringes

Rx only

Pfizer